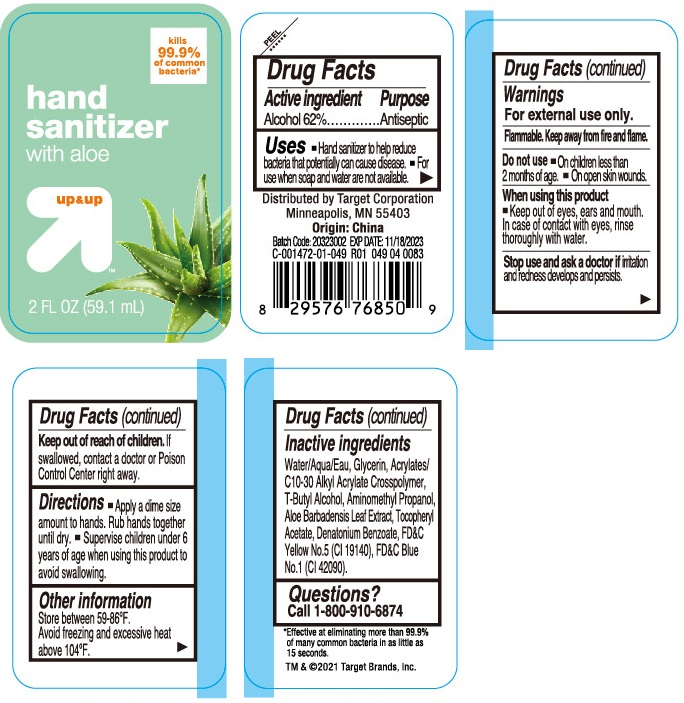 DRUG LABEL: Hand Sanitizer with Aloe
NDC: 11673-082 | Form: LIQUID
Manufacturer: Target Corporation
Category: otc | Type: HUMAN OTC DRUG LABEL
Date: 20201218

ACTIVE INGREDIENTS: ALCOHOL 0.62 mL/1 mL
INACTIVE INGREDIENTS: WATER; GLYCERIN; CARBOMER INTERPOLYMER TYPE A (55000 CPS); TERT-BUTYL ALCOHOL; AMINOMETHYLPROPANOL; ALOE VERA LEAF; .ALPHA.-TOCOPHEROL ACETATE; DENATONIUM BENZOATE; FD&C YELLOW NO. 5; FD&C BLUE NO. 1

Hand Sanitizer with Aloe

Active Ingredient

Alcohol 62%

Purpose

Antiseptic

Use

- Hand snitizer to help reduce bacteria that potentially can cause disease.
- For use when soap and water are not available.

Warnings

For external use only.

Flammable, Keep away from fire and flame

Do not use

- On childern less than 2 months of age.
- On open skin wounds.

When using this product

- Keep out of eyes, ears, and mouth. In case of conatct with eyes, rinse thoroughly with water.

Stop use and ask a doctor if irritation and redness develops and persists.

Keep out of reach of children

If swallowed, conatct a doctor or Poison Control Center right away.

Directions

- Apply a dime size amount to hands. Rub hands together until dry.
- Supervise children under 6 years of age when using this product to avoid swallowing.

Other information

Store between 59-86°F. Avoid freezing and excessive heat above 104°F.

Inactive ingredients

Water/Aqua/Eau, Glycerin, Acrylates/C10-30 Alkyl Acrylate Crosspolymer, T-Butyl Alcohol, Aminomethyl Propanol, Aloe Barbadensis Leaf Extract, Tocopheryl Acetate, Denatonium Benzoate, FD&C Yellow No.5 (CI 19140), FD&C Blue No.1 (CI 42090).

Questions?

Call 1-800-910-6874

Distributed By

Target Corporation

Minneapolis, MN 55403

Package Label

Hand Sanitizer with Aloe

up & up

2 FL OZ (59.1 mL)